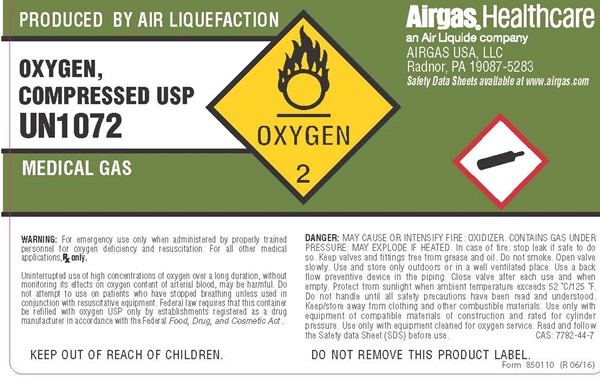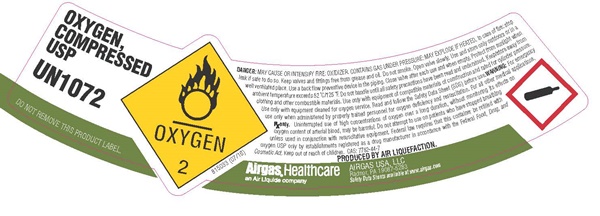 DRUG LABEL: OXYGEN
NDC: 10671-010 | Form: GAS
Manufacturer: Air Liquide America L.P.
Category: prescription | Type: HUMAN PRESCRIPTION DRUG LABEL
Date: 20180928

ACTIVE INGREDIENTS: OXYGEN 99 L/100 L

Oxygen

Oxygen

OXYGEN, COMPRESSED USP

UN1072

DO NOT REMOVE THIS PRODUCT LABEL

OXYGEN 2

81503 (7/16)

DANGER: MAY CAUSE OR INTENSIFY FIRE; OXIDIZER. CONTAINS GAS UNDER PRESSURE. MAY EXPLODE IF HEATED. In cae of fire stop leak if safe to do so. Keep valves and fittings free from grease and oil. Do not smoke. Open valve slowly. Use and store only outdoors or in a well-ventilated place. Use a back-flow preventive device in the piping. Close valve after each use and when empty. Protect from sunlight when ambient temperature exceeds 52OC/125OF. Do not handle until all safety precautions have been read and understood. Keep/store away from clothing and other combustible materials. Use only with equipment of compatible materials of construction and rated for cylinder pressure. Use only with equipment clean d for oxygen service. Read and follow the Safety Data Sheet (SDS) before use. WARNING: For emergency use only when administered by properly trained personnel for oxygen deficiency and resuscitation. For all other medical applications. Rx only. Uninterrupted use of high concentrations of oxygen over a long duration, without monitoring its effect on oxygen content of arterial blood, may be harmful. Do not attempt to use on patients who have stopped breathing unless used in conjunction with resuscitative equipment. Federal law requires that this container be refilled with oxygen USP only by establishments registered as a drug manufacture in accordance with the Federal Food, Drug, and Cosmetic Act. Keep out of reach of children. CAS 7782-44-7

PRODUCED BY AIR LIQUIEFACTION.

Airgas, Healthcare

an Air Liquide Company

AIRGAS USA LLC

Radnor, PA 19087-5283

Safety Data Sheets available at www.airgas.com